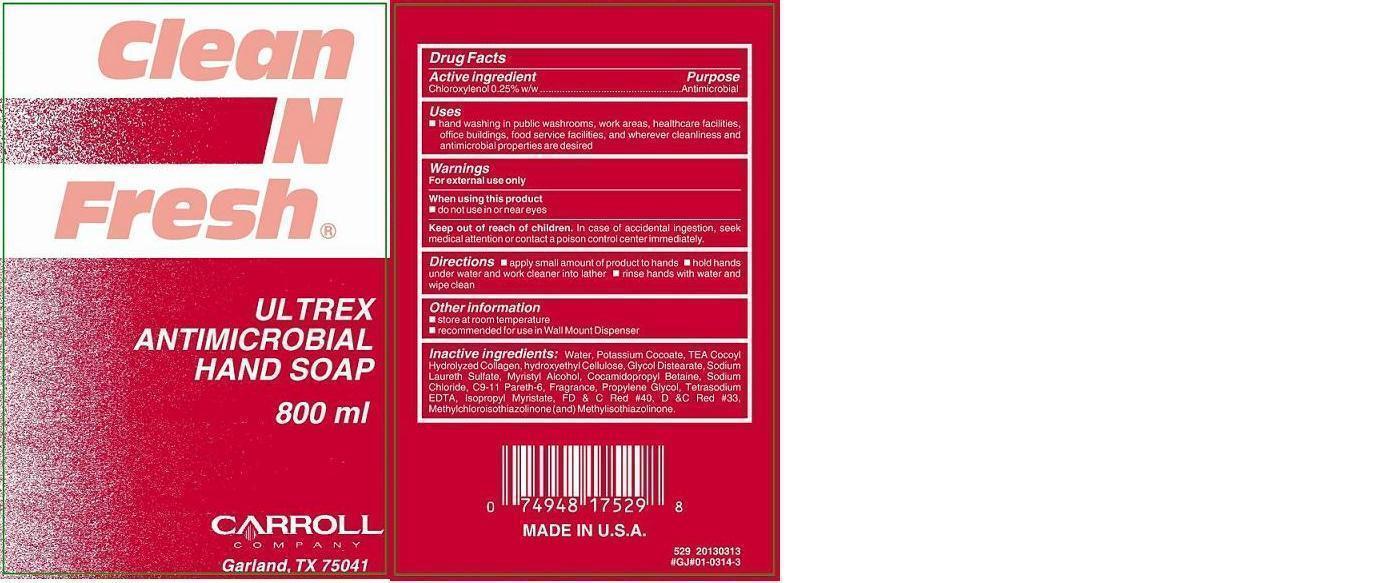 DRUG LABEL: PC529 ULTREX
NDC: 10685-529 | Form: SOAP
Manufacturer: CARROLL COMPANY
Category: otc | Type: HUMAN OTC DRUG LABEL
Date: 20180131

ACTIVE INGREDIENTS: CHLOROXYLENOL 2.5 g/1000 mL
INACTIVE INGREDIENTS: WATER; GLYCOL DISTEARATE; MYRISTYL ALCOHOL; C9-11 PARETH-6; SODIUM LAURETH SULFATE; PROPYLENE GLYCOL; ISOPROPYL MYRISTATE; METHYLCHLOROISOTHIAZOLINONE; METHYLISOTHIAZOLINONE; COCAMIDOPROPYL BETAINE; HYDROXYETHYL CELLULOSE (5000 MPA.S AT 1%); POTASSIUM COCOATE; EDETATE SODIUM; SODIUM CHLORIDE; CITRIC ACID MONOHYDRATE

Active ingredient

Chloroxylenol 0.25% w/w

Purpose

Antimicrobial

Keep out of reach of children

In case of accidental ingestion, seek medical attention or contact a poison control center immediately.

Uses

Hand washing in public washrooms, work areas, healthcare facilities,

ofice buildings, food service facilities, and wherever cleanliness and

antimicrobial properties are desired.

Warnings

For external use only

When using this product

- do not use in or near eyes

Directions

 apply small amount of product to hands.  hold hands under water and work cleaner into lather.  rinse hands with water and wipe clean.

Other information

 store at room temperature

 recommended for use in Wall Mount Dispenser

Inactive ingredients:

Water, Potassium Cocoate, TEA Cocoyl Hydrolyzed Collagen, hydroxyethyl Cellulose, Glycol Distearate, Sodium Laureth Sulfate, Myristyl Alcohol, Cocamidopropyl Betaine, Sodium Chloride, C9-11 Pareth-6, Fragrance, Propylene Glycol, Tetrasodium EDTA, Isopropyl Myristate, FD & C Red #40, D &C Red #33, Methylchloroisothiazolinone (and) Methylisothiazolinone.